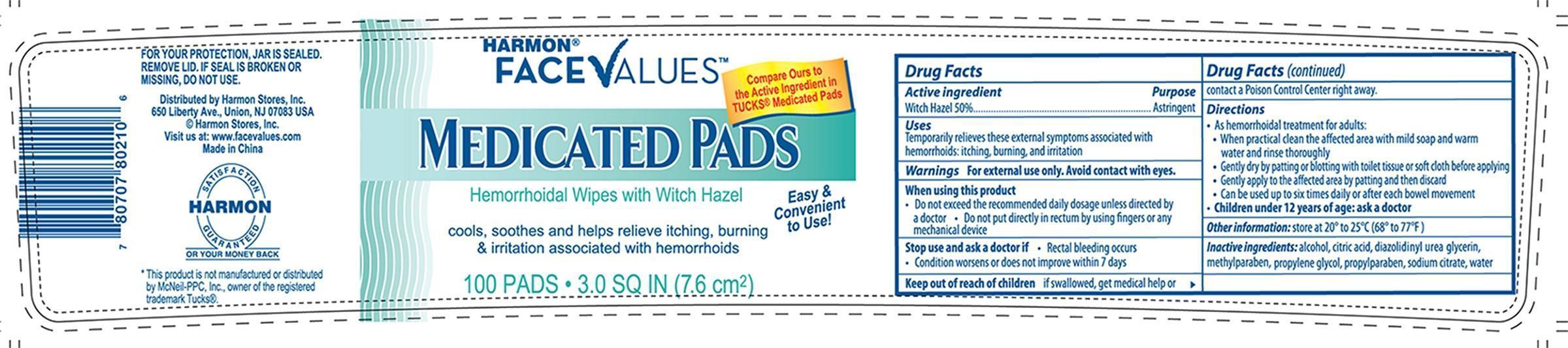 DRUG LABEL: Harmon Face Values Medicated
NDC: 63940-803 | Form: SOLUTION
Manufacturer: Harmon Stores Inc.
Category: otc | Type: HUMAN OTC DRUG LABEL
Date: 20130823

ACTIVE INGREDIENTS: WITCH HAZEL .5 mg/1 mg
INACTIVE INGREDIENTS: ALCOHOL; CITRIC ACID MONOHYDRATE; DIAZOLIDINYL UREA; METHYLPARABEN; PROPYLENE GLYCOL; PROPYLPARABEN; SODIUM CITRATE; WATER

Drug Facts

Active Ingredient Purpose
Witch Hazel 50%................................................................................Astringent

Uses

Temporarily relieves tehse externals ymptoms associated with

hemorrhoids: itching, burning, and irritation

WARNINGS

Warnings For external use only. Avoid contact with eyes.

When using this product

- Do not exceed the recommended daily dosage unless directed by

a doctor - Do not put directly in rectum by using fingers or any

mechanical device

Stop use and ask a doctor if

- Rectal bleeding occrus
- condition worsens or does not improve within 7 days

Keep out of reach of children If swallowed, get medical help or contact a Poison Control Center right away.

Directions

- As hemorrhoidal treatment for adults:
- When practical clean the affected area with mild soap and warm water and rinse thoroughly
- Gentle dry by patting or blotting with toilet tissue or soft cloth before applying
- Gently apply to the afected area by patting and then discard
- Can be used up to six times daily or after each bowel movement
- Children under 12 years of age: ask a doctor

Other Information: store at 20° to 25°C (68° to 77°F)

INACTIVE INGREDIENT

Inactive Ingredients: alcohol, citric acid, diazolidinyl utea glycerin, methylparaben, propylene glycol, propylparaben, sodium citrate, water

DOSAGE AND ADMINISTRATION

Distributed by: Harmon Stores, Inc.

650 Liberty Ave., Union, NJ 07083 USA

Made in China